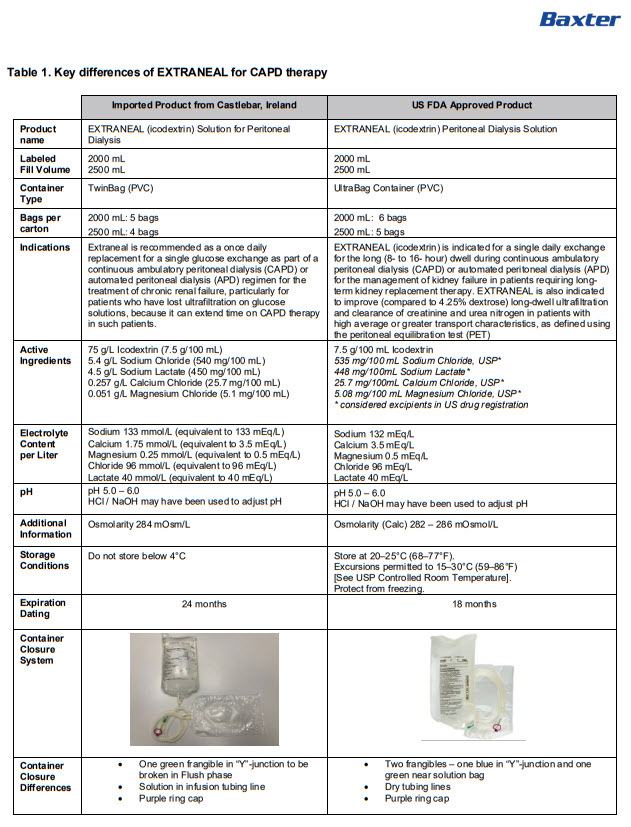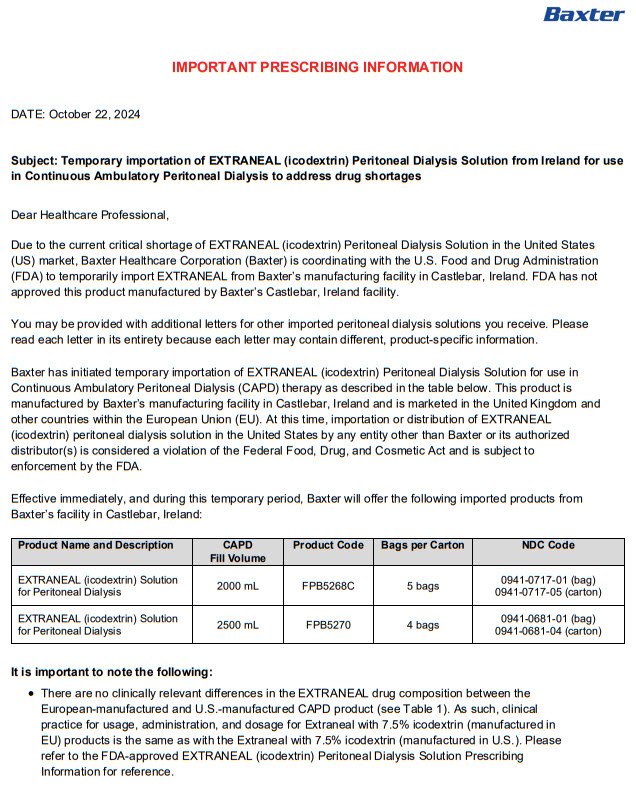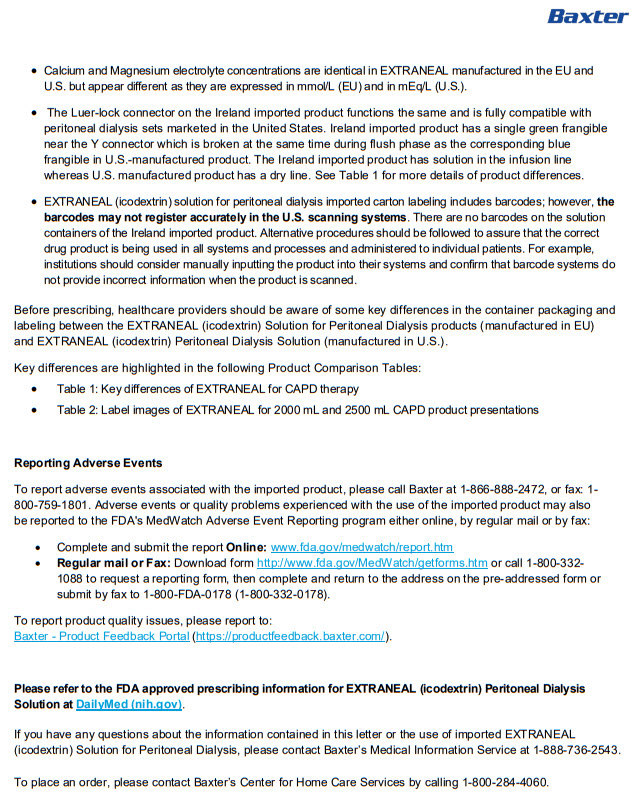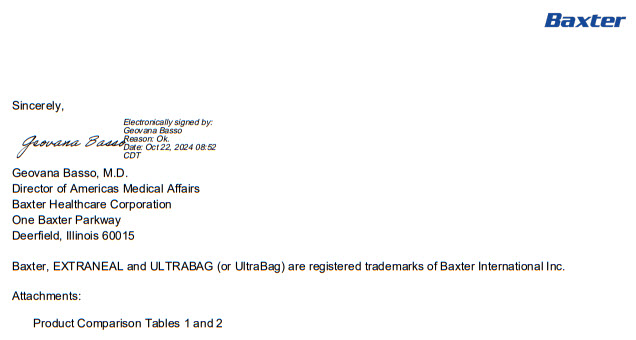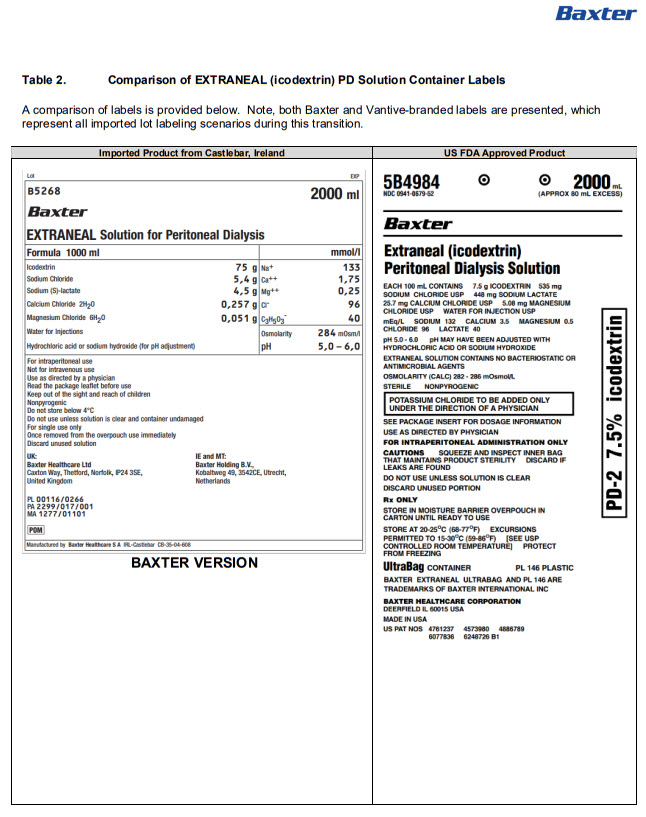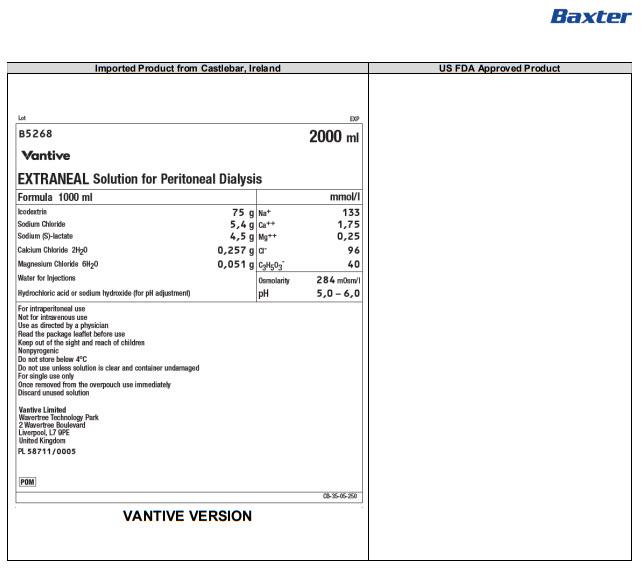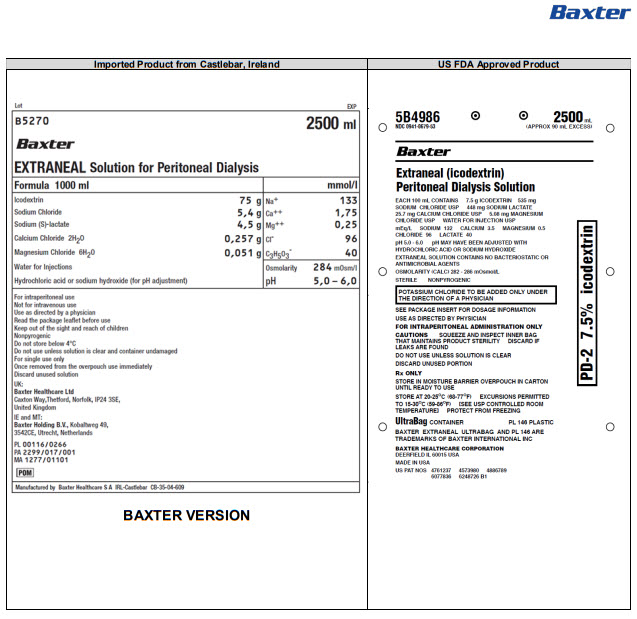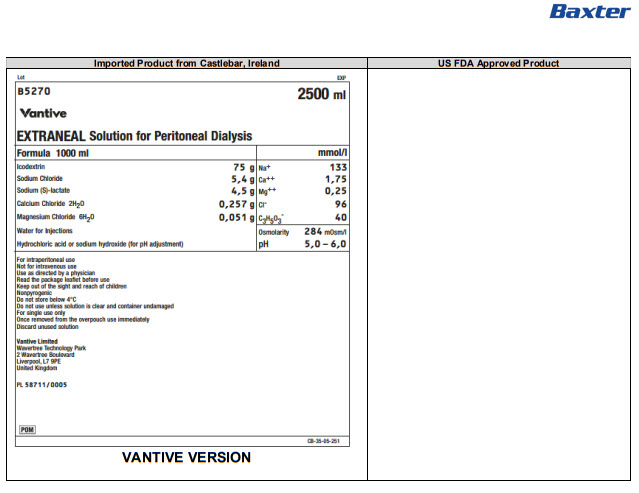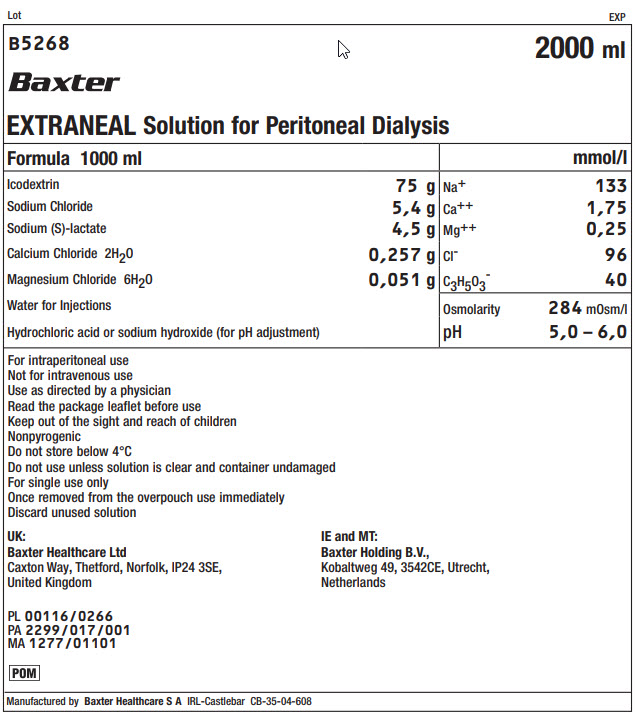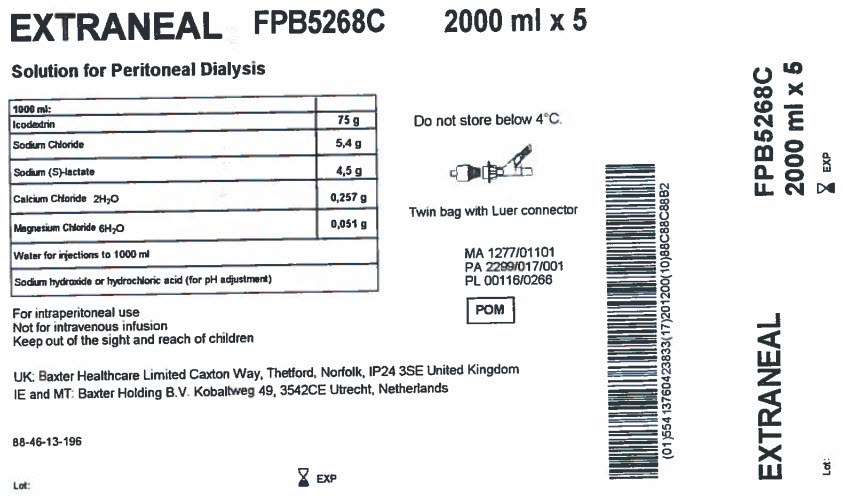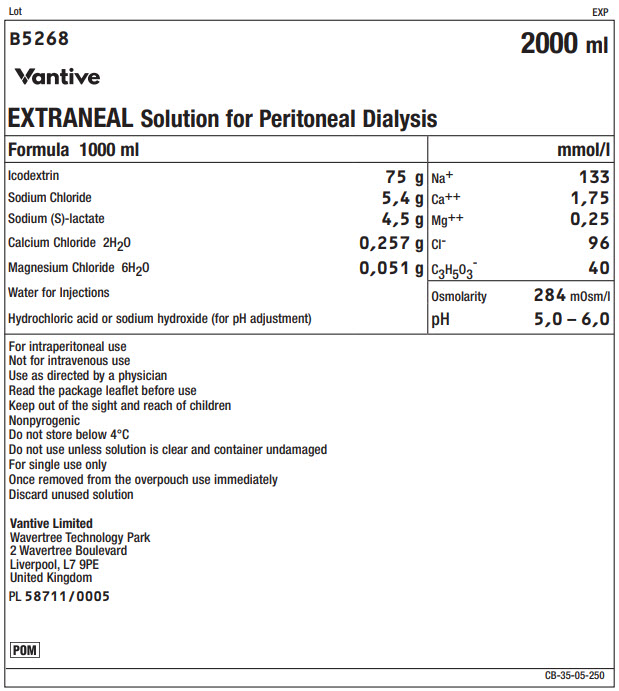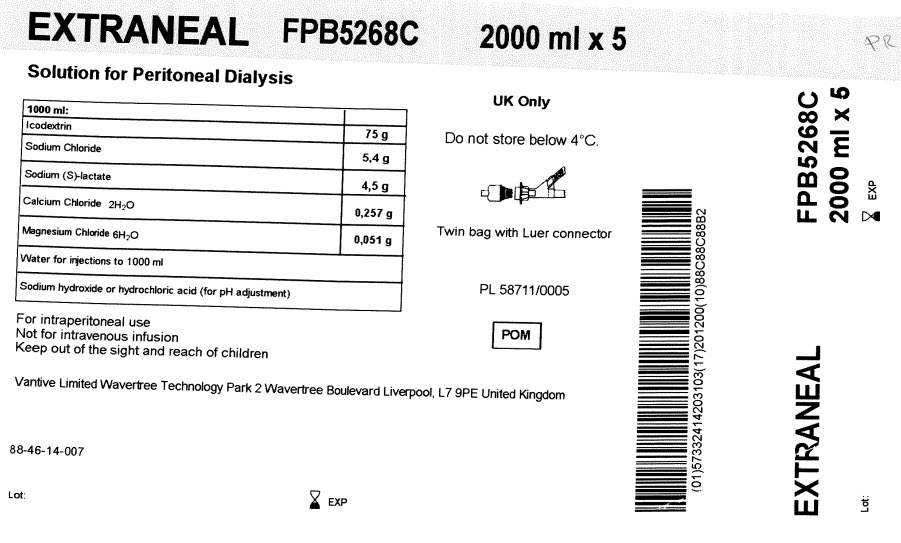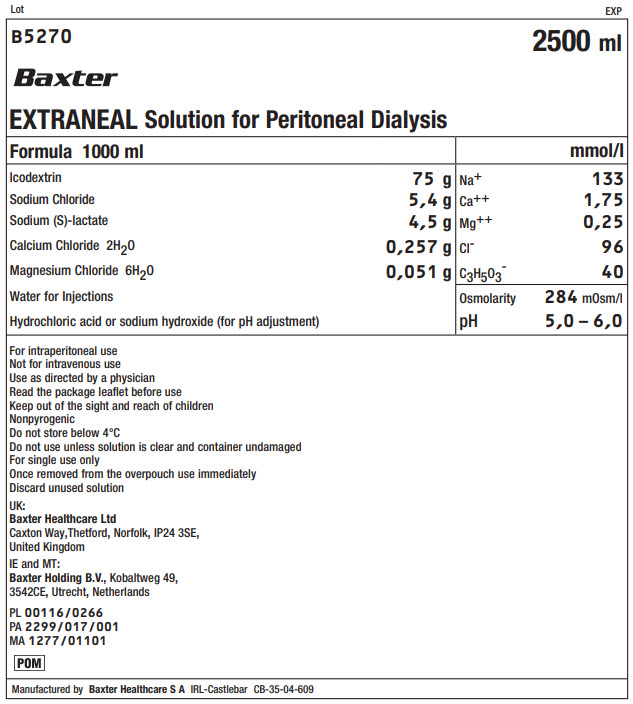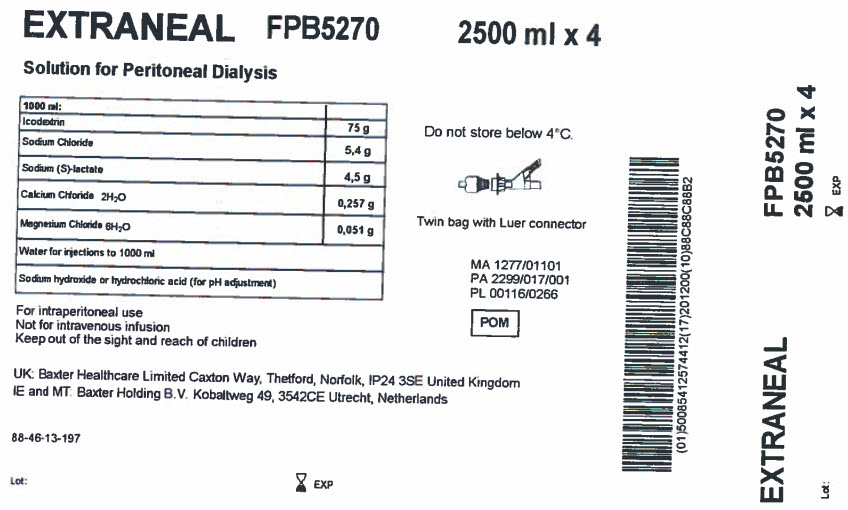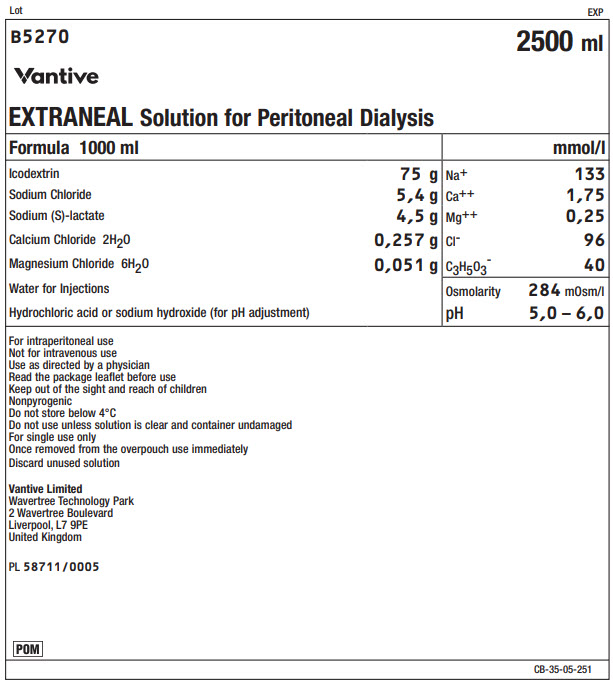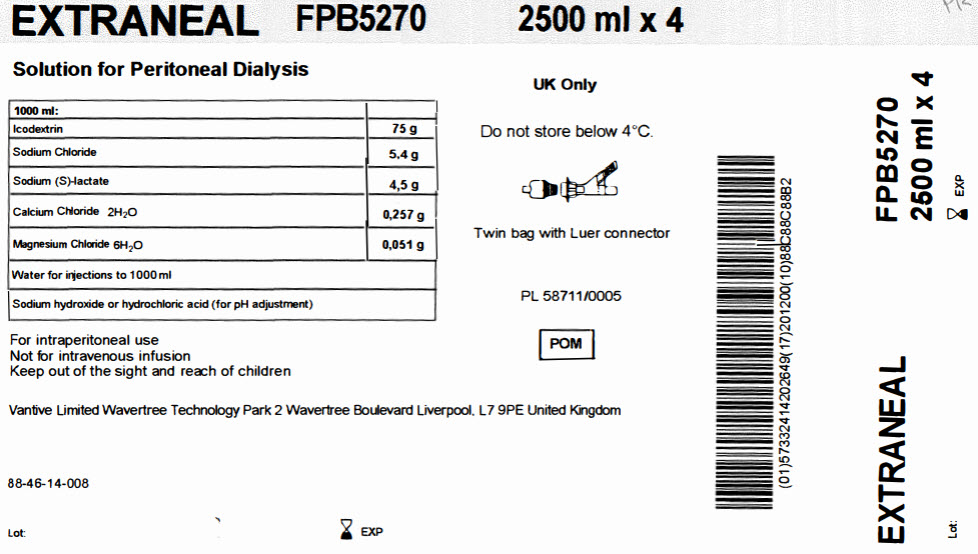 DRUG LABEL: EXTRANEAL
NDC: 0941-0681 | Form: INJECTION, SOLUTION
Manufacturer: Vantive US Healthcare LLC
Category: prescription | Type: HUMAN PRESCRIPTION DRUG LABEL
Date: 20250507

ACTIVE INGREDIENTS: ICODEXTRIN 7.5 g/100 mL; SODIUM CHLORIDE 540 mg/100 mL; SODIUM LACTATE 450 mg/100 mL; CALCIUM CHLORIDE 25.7 mg/100 mL; MAGNESIUM CHLORIDE 5.1 mg/100 mL

EXTRANEAL Solution for Peritoneal Dialysis

PACKAGE/LABEL PRINCIPAL DISPLAY PANEL

Lot EXP
B5268 2000 ml
Baxter
EXTRANEAL Solution for Peritoneal Dialysis

Formula 1000 ml |  | mmol/l
Icodextrin | 75 g | Na+ | 133
Sodium Chloride | 5,4 g | Ca++ | 1,75
Sodium (S)-lactate | 4,5 g | Mg++ | 0,25
Calcium Chloride 2H20 | 0,257 g | Clˉ | 96
Magnesium Chloride 6H20 | 0,051 g | C3H503ˉ | 40
Water for Injections |  | Osmolarity | 284mOsm/l
Hydrochloric acid or sodium hydroxide (for pH adjustment) |  | pH | 5,0 – 6,0

For intraperitoneal use
Not for intravenous use
Use as directed by a physician
Read the package leaflet before use
Keep out of the sight and reach of children
Nonpyrogenic
Do not store below 4°C
Do not use unless solution is clear and container undamaged
For single use only
Once removed from the overpouch use immediately
Discard unused solution

UK:
Baxter Healthcare Ltd
Caxton Way, Thetford, Norfolk, IP24 3SE,
United Kingdom

IE and MT:
Baxter Holding B.V.,
Kobaltweg 49, 3542CE, Utrecht,
Netherlands

PL 00116/0266
PA 2299/017/001
MA 1277/01101

POM Symbol

Manufactured by Baxter Healthcare S A IRL-Castlebar CB-35-04-608

EXTRANEAL
FPB5268C
2000 ml x 5

Solution for Peritoneal Dialysis

1000 ml
Icodextrin | 75 g
Sodium Chloride | 5,4 g
Sodium (S)-lactate | 4,5 g
Calcium Chloride 2H20 | 0,257 g
Magnesium Chloride 6H20 | 0,051 g
Water for injections to 1000 ml
Sodium hydroxide or hydrochloric acid (for pH adjustment)

For intraperitoneal use
Not for intravenous infusion
Keep out of the sight and reach of children

UK: Baxter Healthcare Limited Caxton Way, Thetford, Norfolk, IP24 3SE United Kingdom
IE and MT: Baxter Holding B.V. Kobaltweg 49, 3542CE, Utrecht, Netherlands

88-46-13-196

Lot: EXP

Do not store below 4°C

Twin bag with Luer connector

MA 1277/01101
PA 2299/017/001
PL 00116/0266

POM Symbol

Barcode
(01)554 13760423833(17)201200(10)88C88C88B2

EXTRANEAL
FPB5268C
2000 ml x 5

Lot: EXP

Lot EXP
B5268 2000 ml
Vantive
EXTRANEAL Solution for Peritoneal Dialysis

Formula 1000 ml |  | mmol/l
Icodextrin | 75 g | Na+ | 133
Sodium Chloride | 5,4 g | Ca++ | 1,75
Sodium (S)-lactate | 4,5 g | Mg++ | 0,25
Calcium Chloride 2H20 | 0,257 g | Clˉ | 96
Magnesium Chloride 6H20 | 0,051 g | C3H503ˉ | 40
Water for Injections |  | Osmolarity | 284mOsm/l
Hydrochloric acid or sodium hydroxide (for pH adjustment) |  | pH | 5,0 – 6,0

For intraperitoneal use
Not for intravenous use
Use as directed by a physician
Read the package leaflet before use
Keep out of the sight and reach of children
Nonpyrogenic
Do not store below 4°C
Do not use unless solution is clear and container undamaged
For single use only
Once removed from the overpouch use immediately
Discard unused solution

Vantive Limited
Wavertree Technology Park
2 Wavertree Boulevard
Liverpool, L7 9PE
United Kingdom

PL 58711/0005

POM Symbol

CB-35-05-250

EXTRANEAL
FPB5268C
2000 ml x 5

Solution for Peritoneal Dialysis

1000 ml
Icodextrin | 75 g
Sodium Chloride | 5,4 g
Sodium (S)-lactate | 4,5 g
Calcium Chloride 2H20 | 0,257 g
Magnesium Chloride 6H20 | 0,051 g
Water for injections to 1000 ml
Sodium hydroxide or hydrochloric acid (for pH adjustment)

For intraperitoneal use
Not for intravenous infusion
Keep out of the sight and reach of children

Vantive Limited Wavertree Technology Park 2 Wavertree Boulevard Liverpool, L7 9PE United Kingdom

88-46-14-007

Lot: EXP

UK Only

Do not store below 4°C

Twin bag with Luer connector

PL 58711/0005

POM Symbol

Barcode
(01)57332414203103 (17)201200(10)88C88C88B2

EXTRANEAL
FPB5268C
2000 ml x 5

Lot: EXP

Lot EXP
B5270 2500 ml
Baxter
EXTRANEAL Solution for Peritoneal Dialysis

Formula 1000 ml |  | mmol/l
Icodextrin | 75 g | Na+ | 133
Sodium Chloride | 5,4 g | Ca++ | 1,75
Sodium (S)-lactate | 4,5 g | Mg++ | 0,25
Calcium Chloride 2H20 | 0,257 g | Clˉ | 96
Magnesium Chloride 6H20 | 0,051 g | C3H503ˉ | 40
Water for Injections |  | Osmolarity | 284mOsm/l
Hydrochloric acid or sodium hydroxide (for pH adjustment) |  | pH | 5,0 – 6,0

For intraperitoneal use
Not for intravenous use
Use as directed by a physician
Read the package leaflet before use
Keep out of the sight and reach of children
Nonpyrogenic
Do not store below 4°C
Do not use unless solution is clear and container undamaged
For single use only
Once removed from the overpouch use immediately
Discard unused solution

UK:
Baxter Healthcare Ltd
Caxton Way, Thetford, Norfolk, IP24 3SE,
United Kingdom

IE and MT:
Baxter Holding B.V., Kobaltweg 49,
3542CE, Utrecht, Netherlands

PL 00116/0266
PA 2299/017/001
MA 1277/01101

POM Symbol

Manufactured by Baxter Healthcare S A IRL-Castlebar CB-35-04-609

EXTRANEAL
FPB5270
2500 ml x 4

Solution for Peritoneal Dialysis

1000 ml
Icodextrin | 75 g
Sodium Chloride | 5,4 g
Sodium (S)-lactate | 4,5 g
Calcium Chloride 2H20 | 0,257 g
Magnesium Chloride 6H20 | 0,051 g
Water for injections to 1000 ml
Sodium hydroxide or hydrochloric acid (for pH adjustment)

For intraperitoneal use
Not for intravenous infusion
Keep out of the sight and reach of children

UK: Baxter Healthcare Limited Caxton Way, Thetford, Norfolk, IP24 3SE United Kingdom
IE and MT: Baxter Holding B.V. Kobaltweg 49, 3542CE, Utrecht, Netherlands

88-46-13-197

Lot: EXP

Do not store below 4°C

Twin bag with Luer connector

MA 1277/01101
PA 2299/017/001
PL 00116/0266

POM Symbol

Barcode
(01)50085412574412(17)201200(10)88C88C88B2

EXTRANEAL
FPB5270
2000 ml x 4

Lot: EXP

Lot EXP
B5270 2500 ml
Vantive
EXTRANEAL Solution for Peritoneal Dialysis

Formula 1000 ml |  | mmol/l
Icodextrin | 75 g | Na+ | 133
Sodium Chloride | 5,4 g | Ca++ | 1,75
Sodium (S)-lactate | 4,5 g | Mg++ | 0,25
Calcium Chloride 2H20 | 0,257 g | Clˉ | 96
Magnesium Chloride 6H20 | 0,051 g | C3H503ˉ | 40
Water for Injections |  | Osmolarity | 284mOsm/l
Hydrochloric acid or sodium hydroxide (for pH adjustment) |  | pH | 5,0 – 6,0

For intraperitoneal use
Not for intravenous use
Use as directed by a physician
Read the package leaflet before use
Keep out of the sight and reach of children
Nonpyrogenic
Do not store below 4°C
Do not use unless solution is clear and container undamaged
For single use only
Once removed from the overpouch use immediately
Discard unused solution

Vantive Limited
Wavertree Technology Park
2 Wavertree Boulevard
Liverpool, L7 9PE
United Kingdom

PL 58711/0005

POM Symbol

CB-35-05-251

EXTRANEAL
FPB5270
2500 ml x 4

Solution for Peritoneal Dialysis

1000 ml
Icodextrin | 75 g
Sodium Chloride | 5,4 g
Sodium (S)-lactate | 4,5 g
Calcium Chloride 2H20 | 0,257 g
Magnesium Chloride 6H20 | 0,051 g
Water for injections to 1000 ml
Sodium hydroxide or hydrochloric acid (for pH adjustment)

For intraperitoneal use
Not for intravenous infusion
Keep out of the sight and reach of children

Vantive Limited Wavertree Technology Park 2 Wavertree Boulevard Liverpool, L7 9PE United Kingdom

88-46-14-008

Lot: EXP

UK Only

Do not store below 4°C

Twin bag with Luer connector

PL 58711/0005

POM Symbol

Barcode
(01)57332414202649 (17)201200(10)88C88C88B2

EXTRANEAL
FPB5270

2500 ml x 4

Lot: EXP